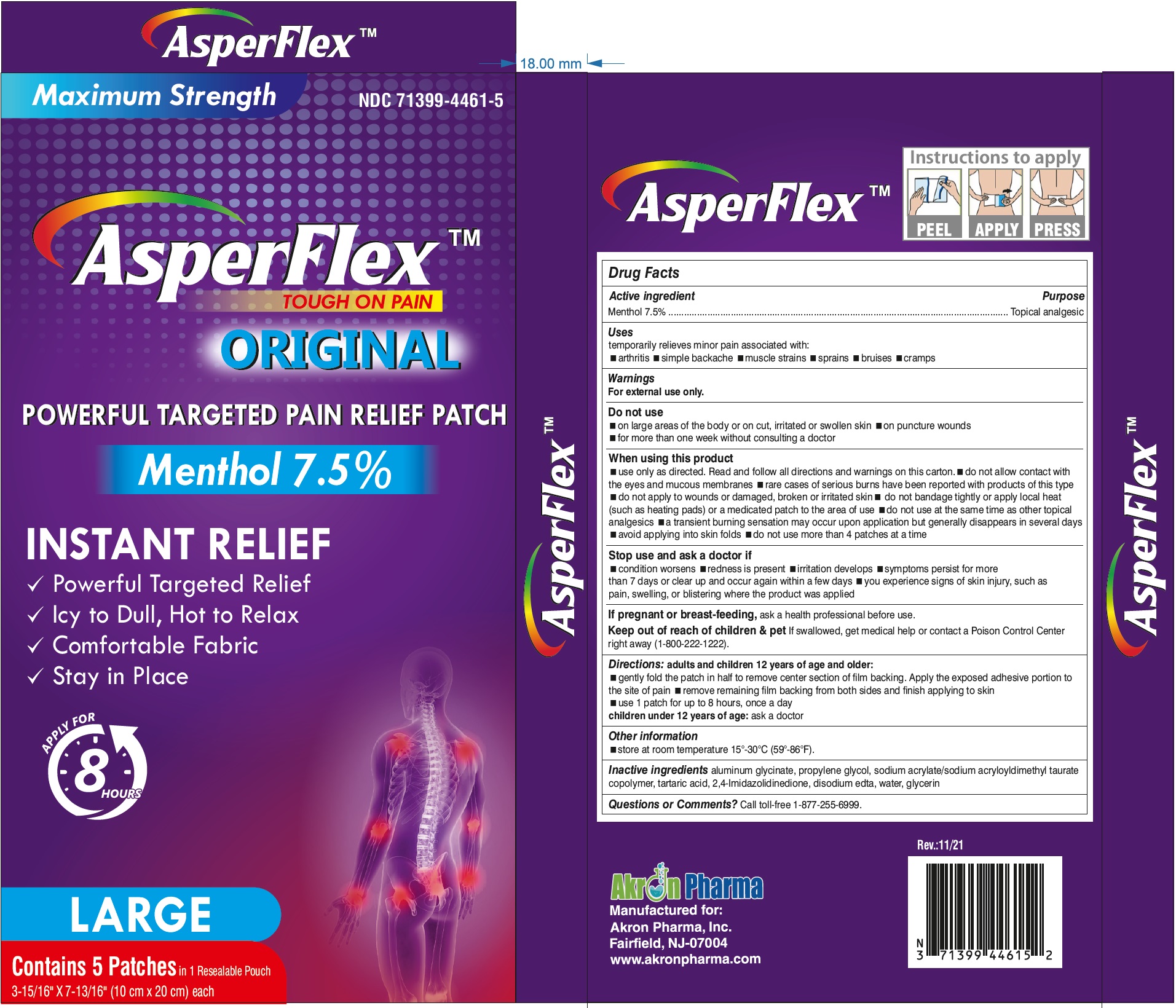 DRUG LABEL: AsperFlex Original Maximum Strength
NDC: 71399-4461 | Form: PATCH
Manufacturer: Akron Pharma Inc.
Category: otc | Type: HUMAN OTC DRUG LABEL
Date: 20251002

ACTIVE INGREDIENTS: MENTHOL 210 mg/1 1
INACTIVE INGREDIENTS: DIHYDROXYALUMINUM AMINOACETATE ANHYDROUS; PROPYLENE GLYCOL; SODIUM ACRYLATE; TARTARIC ACID; HYDANTOIN; EDETATE DISODIUM ANHYDROUS; WATER; GLYCERIN

Asperflex
Maximum Strength
Tough on Pain
Menthol 7.5% Original

Active Ingredient

Menthol 7.5%

Purpose

Topical analgesic

Uses

for the temporary relief of minor aches and pains of muscles and joints associated with:

■ arthritis ■ simple backache ■ strains ■ sprains ■ bruises

Warnings

For external use only

Do not use

■ on wounds, damaged, broken or irritated skin

■ with a heating pad or apply local heat to the area of use

When using this product

- use only as directed. Read and follow all directions and warnings on this carton.
- do not allow contact with
- the eyes and mucous membranes
- rare cases of serious burns have been reported with products of this type
- do not apply to wounds or damaged, broken or irritated skin
- do not bandage tightly or apply local heat (such as heating pads) or a medicated patch to the area of use
- do not use at the same time as other topical analgesics
- a transient burning sensation may occur upon application but generally disappears in several days
- avoid applying into skin folds <do not use more than 4 patches at a time

Stop use and ask a doctor if

■condition worsens or symptoms persist for more than 7 days

■ symptoms clear up and occur again within a few days

■ severe burning sensation, redness or irritation develop

■ you experience signs of skin injury, such as pain, swelling, or blistering where the product was applied

If pregnant or breast-feeding,

ask a health professional before use.

Keep out of reach of children.

If swallowed, get medical help or contact a Poison Control Center right away (1-800-222-1222).

Directions

adults and children 12 years of age and older:

■ gently fold the patch in half to remove center section of film backing. Apply the exposed adhesive portion to the site of pain.

■ remove remaining film backing from both sides and finish applying to skin

■ apply to affected area not more than 3 to 4 times daily

children under 12 years of age:consult a doctor

Other Information

store at room temperature 15°-30°C (59°-86°F).

Inactive ingredients

aluminum glycinate, propylene glycol, sodium acrylate/sodium acryloyldimethyl taurate copolymer, tartaric acid, 2,4-Imidazolidinedione, disodium edta, water, glycerin

Questions or Comments?

Call toll-free 1-877-255-6999.